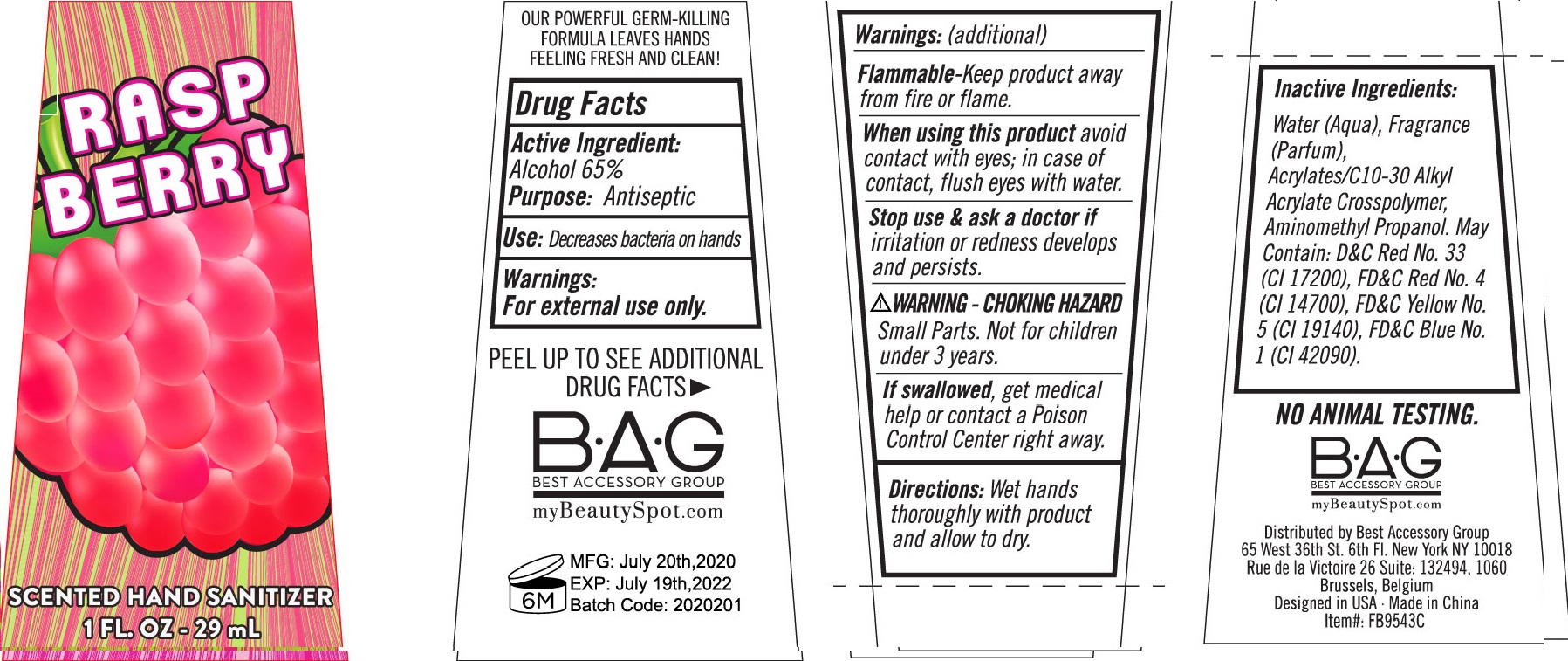 DRUG LABEL: Hand Sanitizer Rasp Berry Scented
NDC: 56136-340 | Form: GEL
Manufacturer: Ganzhou Olivee Cosmetic Co., Ltd.
Category: otc | Type: HUMAN OTC DRUG LABEL
Date: 20200625

ACTIVE INGREDIENTS: ALCOHOL 65 mL/100 mL
INACTIVE INGREDIENTS: WATER; CARBOMER COPOLYMER TYPE A; AMINOMETHYLPROPANOL; .ALPHA.-TOCOPHEROL ACETATE, DL-

HAND SANITIZER

Active ingredient

Alcohol 65%

Purpose

Antiseptic

Use

Decreases bacteria on hands

Warnings

For external use only.

Flammable. Keep product away from fire or flame.

When using this product avoid contact with eyes. In case of contact flush eyes with water.

Stop use and ask a doctor if irritation orredness develops and persists.

Choking Hazard

small parts. Not for children under 3 years.

Keep out of reach of children.

If swallowed, get medical help or contact a Poison Control Center right away.

Directions

Wet hands thoroughly with product and allow to dry.

Inactive ingredients

Water (Aqua), Fragrance (Parfum), Acrylates/C10-30 Alkyl Acrylate Crosspolymer, Aminomethyl Propanol. May contain: D&C Red No. 33 (Cl 17200), FD&C Red No. 4 (CI 14700), FD&C Yellow No. 5 (Cl 19140), FD&C Blue No. 1 (Cl 42090).